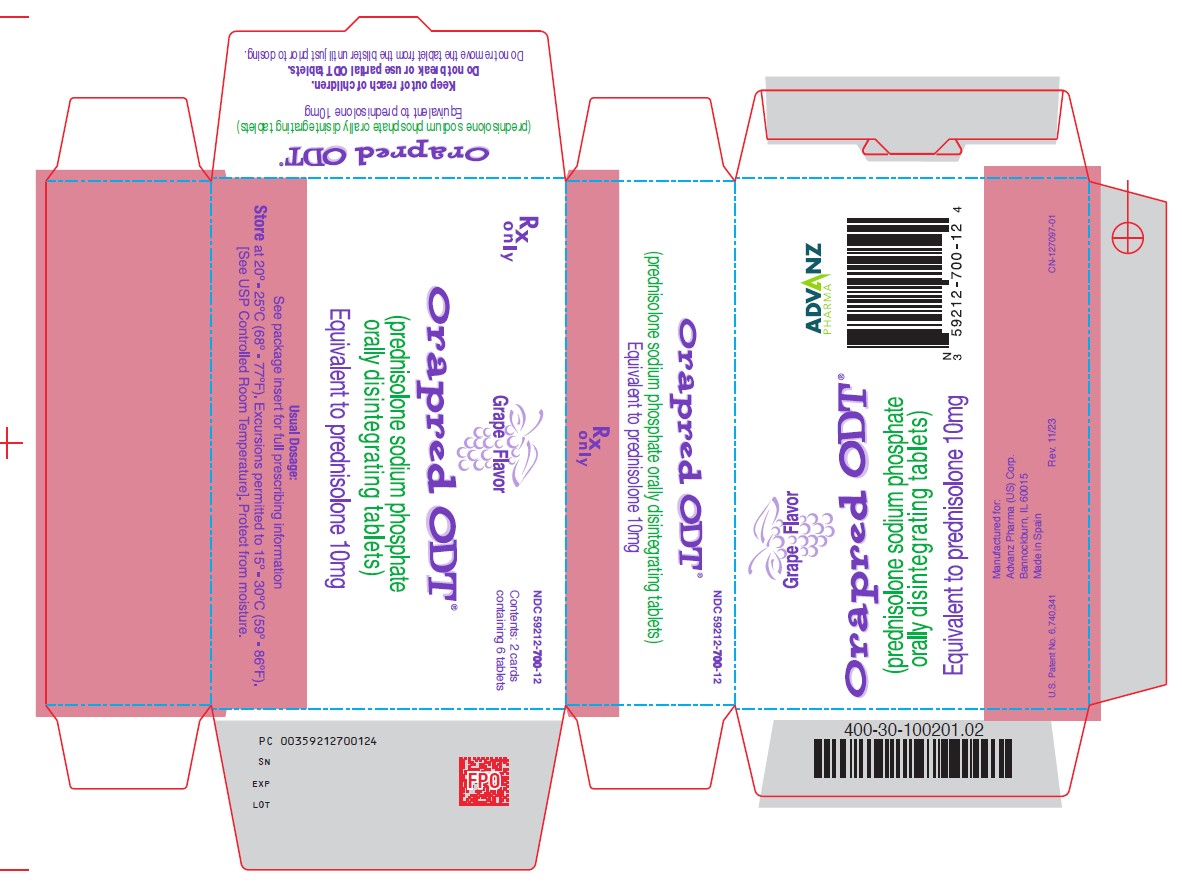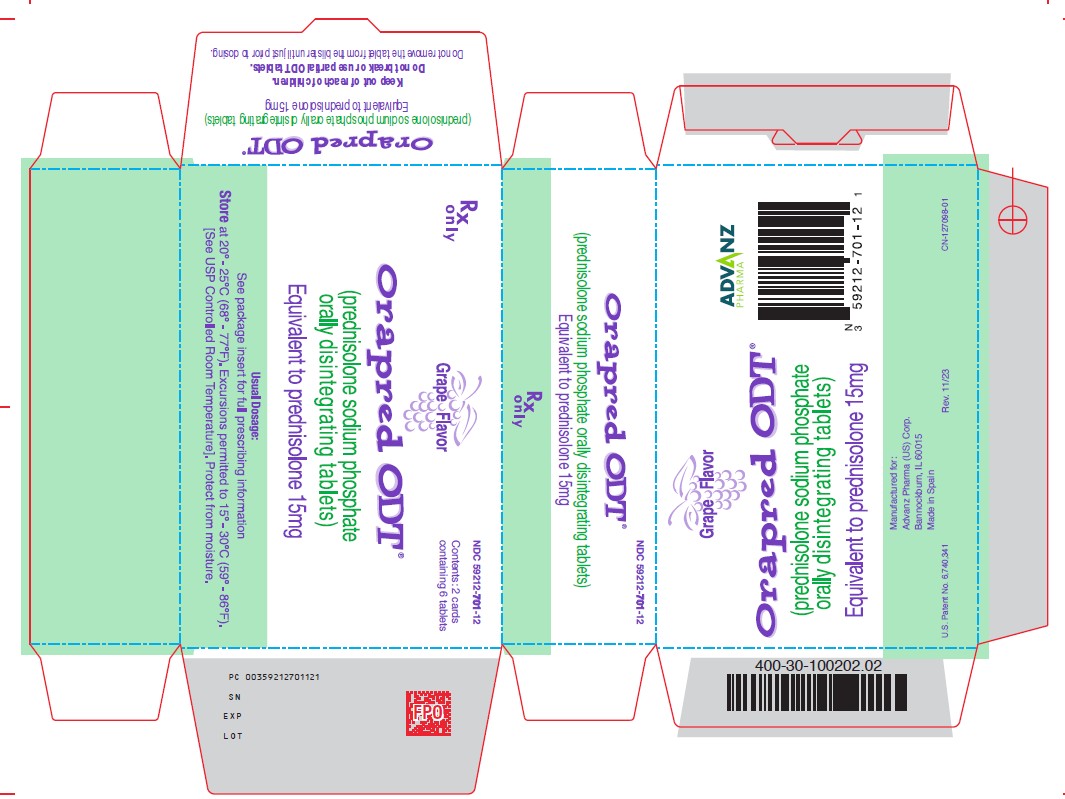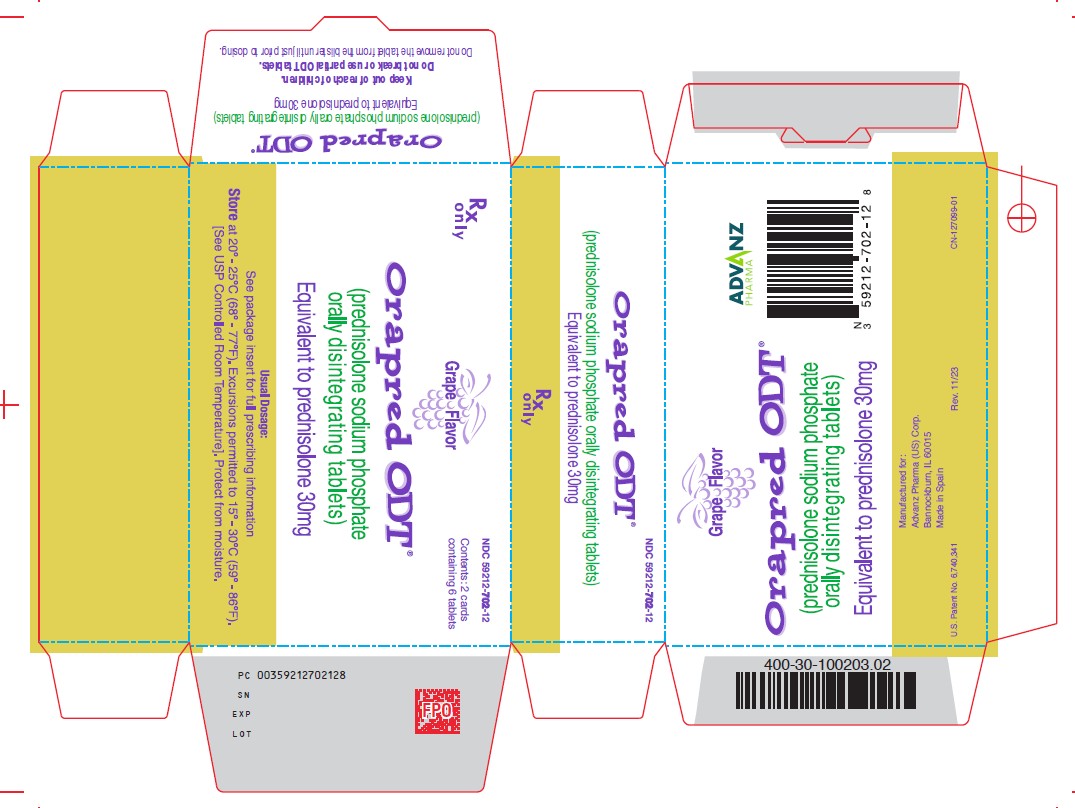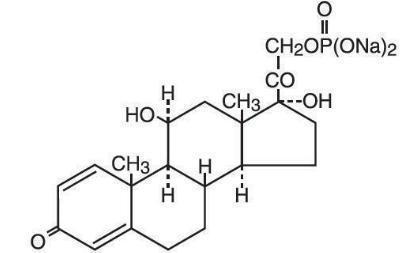 DRUG LABEL: Orapred
NDC: 59212-700 | Form: TABLET, ORALLY DISINTEGRATING
Manufacturer: Advanz Pharma (US) Corp.
Category: prescription | Type: Human Prescription Drug Label
Date: 20250603

ACTIVE INGREDIENTS: PREDNISOLONE SODIUM PHOSPHATE 10 mg/1 1
INACTIVE INGREDIENTS: CITRIC ACID MONOHYDRATE; SILICON DIOXIDE; CROSPOVIDONE; HYPROMELLOSES; MAGNESIUM STEARATE; MANNITOL; CELLULOSE, MICROCRYSTALLINE; SODIUM BICARBONATE; SUCRALOSE; SUCROSE; DIMETHYLAMINOETHYL METHACRYLATE - BUTYL METHACRYLATE - METHYL METHACRYLATE COPOLYMER

HIGHLIGHTS OF PRESCRIBING INFORMATION

These highlights do not include all the information needed to use ORAPRED ODT® safely and effectively. See full prescribing information for ORAPRED ODT®.
ORAPRED ODT® (prednisolone sodium phosphate orally disintegrating tablets)
Initial U.S. Approval: 1955

RECENT MAJOR CHANGES

Immunosuppression and Increased Risk of Infection (5.2) 3/2024

1 INDICATIONS AND USAGE

Orapred ODT is a corticosteroid indicated

- as an anti-inflammatory or immunosuppressive agent for certain allergic, dermatologic, gastrointestinal, hematologic, ophthalmologic, nervous system, renal, respiratory, rheumatologic, specific infectious diseases or conditions and organ transplantation (1)
- for the treatment of certain endocrine conditions (1)
- for palliation of certain neoplastic conditions (1)

2 DOSAGE AND ADMINISTRATION

Individualize dosing based on disease severity and patient response:

- Initial Dose: 10 mg to 60 mg of prednisolone (as 13.4 mg to 80.6 mg of prednisolone sodium phosphate) (2)
- Maintenance Dose: Use lowest dosage that will maintain an adequate clinical response (2)
- Discontinuation: Withdraw gradually if discontinuing long-term or high-dose therapy (2)
- Take with food to avoid gastrointestinal (GI) irritation (2)

DO NOT BREAK OR USE PARTIAL ORAPRED ODT TABLETS. USE AN APPROPRIATE FORMULATION OF PREDNISOLONE IF INDICATED DOSE CANNOT BE OBTAINED USING ORAPRED ODT. (2)

3 DOSAGE FORMS AND STRENGTHS

Orally Disintegrating Tablets:

- 10 mg Tablets (as 13.4 mg prednisolone sodium phosphate) (3)
- 15 mg Tablets (as 20.2 mg prednisolone sodium phosphate) (3)
- 30 mg Tablets (as 40.3 mg prednisolone sodium phosphate) (3)

4 CONTRAINDICATIONS

- Hypersensitivity to prednisolone or any components of this product. (4)

5 WARNINGS AND PRECAUTIONS

- Hypothalamic-pituitary-adrenal (HPA) axis suppression, Cushing's syndrome and hyperglycemia: Monitor patients for these conditions with chronic use. Taper doses gradually for withdrawal after chronic use. (5.1)
- Immunosuppression and Increased Risk of Infection: Increased susceptibility to new infection and increased risk of exacerbation, dissemination, or reactivation of latent infection. Signs and symptoms of infection may be masked. (5.2)
- Elevated blood pressure, salt and water retention and hypokalemia: Monitor blood pressure and sodium, potassium serum levels. (5.3)
- GI perforation: increased risk in patients with certain GI disorders. Signs and symptoms may be masked. (5.4)
- Behavioral and mood disturbances: May include euphoria, insomnia, mood swings, personality changes, severe depression, and psychosis. Existing conditions may be aggravated. (5.5)
- Decrease in bone density: Monitor bone density in patients receiving long term corticosteroid therapy. (5.6)
- Ophthalmic effects: May include cataracts, infections and glaucoma. Monitor intraocular pressure if corticosteroid therapy is continued for more than 6 weeks. (5.7)
- Live or live attenuated vaccines: Do not administer to patients receiving immunosuppressive doses of corticosteroids. (5.8)
- Negative effects on growth and development: Monitor pediatric patients on long-term corticosteroid therapy. (5.9)
- Embryo-Fetal Toxicity: Can cause fetal harm with first trimester use. Advise patients of potential harm to the fetus. (5.10)

6 ADVERSE REACTIONS

Common adverse reactions for corticosteroids include fluid retention, alteration in glucose tolerance, elevation in blood pressure, behavioral and mood changes, increased appetite and weight gain. (6)

To report SUSPECTED ADVERSE REACTIONS, contact Advanz Pharma (US) Corp. at 1-877-370-1142 or FDA at 1-800-FDA-1088 or www.fda.gov/medwatch.

7 DRUG INTERACTIONS

- Anticoagulant Agents: May enhance or diminish anticoagulant effects. Monitor coagulation indices. (7)
- Antidiabetic Agents: May increase blood glucose concentrations. Dose adjustments of antidiabetic agents may be required. (7)
- CYP 3A4 inducers and inhibitors: May, respectively, increase or decrease clearance of corticosteroids, necessitating dose adjustment. (7)
- Cyclosporine: Increase in activity of both, cyclosporine and corticosteroid when administered concurrently. Convulsions have been reported with concurrent use. (7)
- NSAIDS including aspirin and salicylates: Increased risk of gastrointestinal side effects. (7)

FULL PRESCRIBING INFORMATION

1 INDICATIONS AND USAGE

Orapred ODT (prednisolone sodium phosphate orally disintegrating tablet) is indicated in the treatment of the following diseases or conditions:

1.1 Allergic Conditions

Control of severe or incapacitating allergic conditions intractable to adequate trials of conventional treatment in adult and pediatric populations with:

- Atopic dermatitis
- Drug hypersensitivity reactions
- Seasonal or perennial allergic rhinitis
- Serum sickness

1.2 Dermatologic Diseases

- Bullous dermatitis herpetiformis
- Contact dermatitis
- Exfoliative erythroderma
- Mycosis fungoides
- Pemphigus
- Severe erythema multiforme (Stevens-Johnson syndrome)

1.3 Endocrine Conditions

- Congenital adrenal hyperplasia
- Hypercalcemia of malignancy
- Nonsuppurative thyroiditis
- Primary or secondary adrenocortical insufficiency: hydrocortisone or cortisone is the first choice; synthetic analogs may be used in conjunction with mineralocorticoids where applicable.

1.4 Gastrointestinal Diseases

During acute episodes in:

- Crohn's Disease
- Ulcerative colitis

1.5 Hematologic Diseases

- Acquired (autoimmune) hemolytic anemia
- Diamond-Blackfan anemia
- Idiopathic thrombocytopenic purpura in adults
- Pure red cell aplasia
- Secondary thrombocytopenia in adults

1.6 Neoplastic Conditions

For the treatment of:

- Acute leukemia
- Aggressive lymphomas

1.7 Nervous System Conditions

- Acute exacerbations of multiple sclerosis
- Cerebral edema associated with primary or metastatic brain tumor, craniotomy or head injury

1.8 Ophthalmic Conditions

- Sympathetic ophthalmia
- Uveitis and ocular inflammatory conditions unresponsive to topical corticosteroids

1.9 Conditions Related to Organ Transplantation

- Acute or chronic solid organ rejection

1.10 Pulmonary Diseases

- Acute exacerbations of chronic obstructive pulmonary disease (COPD)
- Allergic bronchopulmonary aspergillosis
- Aspiration pneumonitis
- Asthma
- Fulminating or disseminated pulmonary tuberculosis when used concurrently with appropriate chemotherapy
- Hypersensitivity pneumonitis
- Idiopathic bronchiolitis obliterans with organizing pneumonia
- Idiopathic eosinophilic pneumonias
- Idiopathic pulmonary fibrosis Pneumocystis carinii pneumonia (PCP) associated with hypoxemia occurring in an HIV (+) individual who is also under treatment with appropriate anti-PCP antibiotics
- Symptomatic sarcoidosis

1.11 Renal Conditions

To induce a diuresis or remission of proteinuria in nephrotic syndrome, without uremia, of the idiopathic type or that due to lupus erythematosus

1.12 Rheumatologic Conditions

As adjunctive therapy for short term administration (to tide the patient over an acute episode or exacerbation) in:

- Acute gouty arthritis

During an exacerbation or as maintenance therapy in selected cases of:

- Ankylosing spondylitis
- Dermatomyositis /polymyositis
- Polymyalgia rheumatica/temporal arteritis
- Psoriatic arthritis
- Relapsing polychondritis
- Rheumatoid arthritis, including juvenile rheumatoid arthritis (selected cases may require low dose maintenance therapy)
- Sjogren's syndrome
- Systemic lupus erythematosus
- Vasculitis

1.13 Specific Infectious Diseases

- Trichinosis with neurologic or myocardial involvement
- Tuberculous meningitis with subarachnoid block or impending block, used concurrently with appropriate antituberculous chemotherapy

2 DOSAGE AND ADMINISTRATION

2.1 Recommended Dosing

Dosage of Orapred ODT should be individualized according to the severity of the disease and the response of the patient. For pediatric patients, the recommended dosage should be governed by the same considerations rather than strict adherence to the ratio indicated by age or body weight.

Do not break or use partial Orapred ODT tablets. Use an appropriate formulation of prednisolone if indicated dose cannot be obtained using Orapred ODT. This may become important in the treatment of conditions that require tapering doses that cannot be adequately accommodated by Orapred ODT, e.g., tapering the dose below 10 mg.

The initial dose of Orapred ODT may vary from 10 to 60 mg (prednisolone base) per day, depending on the specific disease entity being treated. In situations of less severity, lower doses will generally suffice while in selected patients higher initial doses may be required. The initial dosage should be maintained or adjusted until a satisfactory response is noted. If after a reasonable period of time, there is a lack of satisfactory clinical response, Orapred should be discontinued and the patient placed on other appropriate therapy. IT SHOULD BE EMPHASIZED THAT DOSAGE REQUIREMENTS ARE VARIABLE AND MUST BE INDIVIDUALIZED ON THE BASIS OF THE DISEASE UNDER TREATMENT AND THE RESPONSE OF THE PATIENT. After a favorable response is noted, the proper maintenance dosage should be determined by decreasing the initial drug dosage in small decrements at appropriate time intervals until the lowest dosage that will maintain an adequate clinical response is reached. It should be kept in mind that constant monitoring is needed in regard to drug dosage. Included in the situations which may make dosage adjustments necessary are changes in clinical status secondary to remissions or exacerbations in the disease process, the patient's individual drug responsiveness, and the effect of patient exposure to stressful situations not directly related to the disease entity under treatment; in this latter situation it may be necessary to increase the dosage of Orapred ODT for a period of time consistent with the patient's condition. If after long term therapy the drug is to be stopped, it is recommended that it be withdrawn gradually rather than abruptly.

Orapred ODT are packaged in a blister. Patients should be instructed not to remove the tablet from the blister until just prior to dosing. The blister pack should then be peeled open, and the orally disintegrating tablet placed on the tongue, where tablets may be swallowed whole as any conventional tablet, or allowed to dissolve in the mouth, with or without the assistance of water. Orally disintegrating tablet dosage forms are friable and are not intended to be cut, split, or broken.

Multiple Sclerosis
In the treatment of acute exacerbations of multiple sclerosis, daily doses of 200 mg of prednisolone for a week followed by 80 mg every other day for one month have been shown to be effective.

Pediatric
In pediatric patients, the initial dose of Orapred may vary depending on the specific disease entity being treated. The range of initial doses is 0.14 to 2 mg/kg/day in three or four divided doses (4 to 60 mg/m^2bsa/day).

Nephrotic Syndrome
The standard regimen used to treat nephrotic syndrome in pediatric patients is 60 mg/m^2/day given in three divided doses for 4 weeks, followed by 4 weeks of single dose alternate-day therapy at 40 mg/m^2/day.

Asthma
The National Heart, Lung, and Blood Institute (NHLBI) recommended dosing for systemic prednisone, prednisolone or methylprednisolone in children whose asthma is uncontrolled by inhaled corticosteroids and long-acting bronchodilators is 1-2 mg/kg/day in single or divided doses.

It is further recommended that short course, or "burst" therapy, be continued until a child achieves a peak expiratory flow rate of 80% of his or her personal best or symptoms resolve. This usually requires 3 to 10 days of treatment, although it can take longer. There is no evidence that tapering the dose after improvement will prevent a relapse.

2.2 Recommended Monitoring

Blood pressure, body weight, routine laboratory studies, including serum potassium and fasting blood glucose, should be obtained at regular intervals during prolonged therapy. Appropriate diagnostic studies should be performed in patients with known or suspected peptic ulcer disease and in patients at risk for reactivation of latent tuberculosis infections.

2.3 Corticosteroid Comparison Chart

For the purpose of comparison, one 10 mg Orapred ODT tablet (13.4 mg prednisolone sodium phosphate) is equivalent to the following milligram dosage of the various glucocorticoids:

Betamethasone 1.75 mg | Paramethasone 4 mg
Cortisone 50 mg | Prednisolone 10 mg
Dexamethasone 1.75 mg | Prednisone 10 mg
Hydrocortisone 40 mg | Triamcinolone 8 mg
Methylprednisolone 8 mg

These dose relationships apply only to oral or intravenous administration of these compounds. When these substances or their derivatives are injected intramuscularly or into joint spaces, their relative properties may be greatly altered.

3 DOSAGE FORMS AND STRENGTHS

Orally disintegrating tablets:

- 10 mg prednisolone (as 13.4 mg prednisolone sodium phosphate)
- 15 mg prednisolone (as 20.2 mg prednisolone sodium phosphate)
- 30 mg prednisolone (as 40.3 mg prednisolone sodium phosphate)

4 CONTRAINDICATIONS

Orapred ODT is contraindicated in patients who are hypersensitive to corticosteroids such as prednisolone or any components of this product. Rare instances of anaphylactoid reactions have occurred in patients receiving corticosteroid therapy.

5 WARNINGS AND PRECAUTIONS

5.1 Alterations in Endocrine Function

Hypothalamic-pituitary-adrenal (HPA) axis suppression, Cushing's syndrome, and hyperglycemia. Monitor patients for these conditions with chronic use.

Corticosteroids can produce reversible HPA axis suppression with the potential for glucocorticosteroid insufficiency after withdrawal of treatment. Drug induced secondary adrenocortical insufficiency may be minimized by gradual reduction of dosage. This type of relative insufficiency may persist for months after discontinuation of therapy; therefore, in any situation of stress occurring during that period, hormone therapy should be reinstituted.

Since mineralocorticoid secretion may be impaired, salt and/or a mineralocorticoid should be administered concurrently. Mineralocorticoid supplementation is of particular importance in infancy.

Metabolic clearance of corticosteroids is decreased in hypothyroid patients and increased in hyperthyroid patients. Changes in thyroid status of the patient may necessitate adjustment in dosage.

5.2 Immunosuppression and Increased Risk of Infection

Corticosteroids, including Orapred ODT, suppress the immune system and increase the risk of infection with any pathogen, including viral, bacterial, fungal, protozoan, or helminthic pathogens. Corticosteroids can:

- Reduce resistance to new infections
- Exacerbate existing infections
- Increase the risk of disseminated infections
- Increase the risk of reactivation or exacerbation of latent infections
- Mask some signs of infection

Corticosteroid-associated infections can be mild but can be severe and at times fatal. The rate of infectious complications increases with increasing corticosteroid dosages.

Monitor for the development of infection and consider Orapred ODT withdrawal or dosage reduction as needed.

Tuberculosis
If Orapred ODT is used to treat a condition in patients with latent tuberculosis or tuberculin reactivity, reactivation of tuberculosis may occur. Closely monitor such patients for reactivation. During prolonged Orapred ODT therapy, patients with latent tuberculosis or tuberculin reactivity should receive chemoprophylaxis.

Varicella Zoster and Measles Viral Infections
Varicella and measles can have a serious or even fatal course in non-immune patients taking corticosteroids, including Orapred ODT. In corticosteroid-treated patients who have not had these diseases or are non-immune, particular care should be taken to avoid exposure to varicella and measles:

- If an Orapred ODT-treated patient is exposed to varicella, prophylaxis with varicella zoster immune globulin may be indicated. If varicella develops, treatment with antiviral agents may be considered.
- If an Orapred ODT-treated patient is exposed to measles, prophylaxis with immunoglobulin may be indicated.

Hepatitis B Virus Reactivation
Hepatitis B virus reactivation can occur in patients who are hepatitis B carriers treated with immunosuppressive dosages of corticosteroids, including Orapred ODT. Reactivation can also occur infrequently in corticosteroid-treated patients who appear to have resolved hepatitis B infection.

Screen patients for hepatitis B infection before initiating immunosuppressive (e.g., prolonged) treatment with Orapred ODT. For patients who show evidence of hepatitis B infection, recommend consultation with physicians with expertise in managing hepatitis B regarding monitoring and consideration for hepatitis B antiviral therapy.

Fungal Infections
Corticosteroids, including Orapred ODT, may exacerbate systemic fungal infections; therefore, avoid Orapred ODT use in the presence of such infections unless Orapred ODT is needed to control drug reactions. For patients on chronic Orapred ODT therapy who develop systemic fungal infections, Orapred ODT withdrawal or dosage reduction is recommended.

Amebiasis
Corticosteroids, including Orapred ODT, may activate latent amebiasis. Therefore, it is recommended that latent amebiasis or active amebiasis be ruled out before initiating Orapred ODT in patients who have spent time in the tropics or patients with unexplained diarrhea.

Strongyloides Infestation
Corticosteroids, including Orapred ODT, should be used with great care in patients with known or suspected Strongyloides (threadworm) infestation. In such patients, corticosteroid-induced immunosuppression may lead to Strongyloides hyperinfection and dissemination with widespread larval migration, often accompanied by severe enterocolitis and potentially fatal gram-negative septicemia.

Cerebral Malaria
Avoid corticosteroids, including Orapred ODT, in patients with cerebral malaria.

5.3 Alterations in Cardiovascular/Renal Function

Corticosteroids can cause elevation of blood pressure, salt and water retention, and increased excretion of potassium and calcium. These effects are less likely to occur with the synthetic derivatives except when used in large doses. Dietary salt restriction and potassium supplementation may be necessary. These agents should be used with caution in patients with hypertension, congestive heart failure, or renal insufficiency.

Literature reports suggest an association between use of corticosteroids and left ventricular free wall rupture after a recent myocardial infarction; therefore, therapy with corticosteroids should be used with caution in these patients.

5.4 Use in Patients with Gastrointestinal Disorders

There is an increased risk of gastrointestinal (GI) perforation in patients with certain GI disorders. Signs of GI perforation, such as peritoneal irritation, may be masked in patients receiving corticosteroids.

Corticosteroids should be used with caution if there is a probability of impending perforation, abscess or other pyogenic infections; diverticulitis; fresh intestinal anastomoses; and active or latent peptic ulcer.

5.5 Behavioral and Mood Disturbances

Corticosteroid use may be associated with central nervous system effects ranging from euphoria, insomnia, mood swings, personality changes, and severe depression, to frank psychotic manifestations. Also, existing emotional instability or psychotic tendencies may be aggravated by corticosteroids.

5.6 Decrease in Bone Density

Corticosteroids decrease bone formation and increase bone resorption both through their effect on calcium regulation (i.e., decreasing absorption and increasing excretion) and inhibition of osteoblast function. This, together with a decrease in the protein matrix of the bone secondary to an increase in protein catabolism, and reduced sex hormone production, may lead to inhibition of bone growth in children and adolescents and the development of osteoporosis at any age. Special consideration should be given to patients at increased risk of osteoporosis (e.g., postmenopausal women) before initiating corticosteroid therapy and bone density should be monitored in patients on long term corticosteroid therapy.

5.7 Ophthalmic Effects

Prolonged use of corticosteroids may produce posterior subcapsular cataracts, glaucoma with possible damage to the optic nerves, and may enhance the establishment of secondary ocular infections due to fungi or viruses.

The use of oral corticosteroids is not recommended in the treatment of optic neuritis and may lead to an increase in the risk of new episodes.

Intraocular pressure may become elevated in some individuals. If steroid therapy is continued for more than 6 weeks, intraocular pressure should be monitored.

Patients with Ocular Herpes Simplex
Corticosteroids should be used cautiously in patients with ocular herpes simplex because of possible corneal perforation. Corticosteroids should not be used in active ocular herpes simplex.

5.8 Vaccination

Administration of live or live attenuated vaccines is contraindicated in patients receiving immunosuppressive doses of corticosteroids. Killed or inactivated vaccines may be administered; however, the response to such vaccines cannot be predicted. Immunization procedures may be undertaken in patients who are receiving corticosteroids as replacement therapy, e.g., for Addison's disease.

While on corticosteroid therapy, patients should not be vaccinated against smallpox. Other immunization procedures should not be undertaken in patients who are on corticosteroids, especially on high dose, because of possible hazards of neurological complications and a lack of antibody response.

5.9 Effect on Growth and Development

Long-term use of corticosteroids can have negative effects on growth and development in children. Growth and development of pediatric patients on prolonged corticosteroid therapy should be carefully monitored.

5.10 Embryo-Fetal Toxicity

Prednisolone can cause fetal harm when administered to a pregnant woman. Human studies suggest a small but inconsistent increased risk of orofacial clefts with use of corticosteroids during the first trimester of pregnancy. Published animal studies show prednisolone to be teratogenic in rats, rabbits, hamsters, and mice with increased incidence of cleft palate in offspring. Intrauterine growth restriction and decreased birth weight have also been reported with corticosteroid use during pregnancy, however, the underlying maternal condition may also contribute to these risks. If this drug is used during pregnancy, or if the patient becomes pregnant while using this drug, advise the patient about the potential harm to the fetus. [see Use in Specific Populations (8.1)].

5.11 Neuromuscular Effects

Although controlled clinical trials have shown corticosteroids to be effective in speeding the resolution of acute exacerbations of multiple sclerosis, they do not show that they affect the ultimate outcome or natural history of the disease. The studies do show that relatively high doses of corticosteroids are necessary to demonstrate a significant effect. [see Dosage and Administration (2)].

An acute myopathy has been observed with the use of high doses of corticosteroids, most often occurring in patients with disorders of neuromuscular transmission (e.g., myasthenia gravis), or in patients receiving concomitant therapy with neuromuscular blocking drugs (e.g., pancuronium). This acute myopathy is generalized, may involve ocular and respiratory muscles, and may result in quadriparesis. Elevation of creatinine kinase may occur. Clinical improvement or recovery after stopping corticosteroids may require weeks to years.

5.12 Kaposi's Sarcoma

Kaposi's sarcoma has been reported to occur in patients receiving corticosteroid therapy, most often for chronic conditions. Discontinuation of corticosteroids may result in clinical improvement of Kaposi’s sarcoma.

6 ADVERSE REACTIONS

Common adverse reactions for corticosteroids include fluid retention, alteration in glucose tolerance, elevation in blood pressure, behavioral and mood changes, increased appetite and weight gain.

Allergic Reactions: Anaphylactoid reaction, anaphylaxis, angioedema

Cardiovascular: Bradycardia, cardiac arrest, cardiac arrhythmias, cardiac enlargement, circulatory collapse, congestive heart failure, fat embolism, hypertension, hypertrophic cardiomyopathy in premature infants, myocardial rupture following recent myocardial infarction, pulmonary edema, syncope, tachycardia, thromboembolism, thrombophlebitis, vasculitis

Dermatologic: Acne, allergic dermatitis, cutaneous and subcutaneous atrophy, dry scalp, edema, facial erythema, hyper or hypo-pigmentation, impaired wound healing, increased sweating, petechiae and ecchymoses, rash, sterile abscess, striae, suppressed reactions to skin tests, thin fragile skin, thinning scalp hair, urticaria

Endocrine: Abnormal fat deposits, decreased carbohydrate tolerance, development of Cushingoid state, hirsutism, manifestations of latent diabetes mellitus and increased requirements for insulin or oral hypoglycemic agents in diabetics, menstrual irregularities, moon facies, secondary adrenocortical and pituitary unresponsiveness (particularly in times of stress, as in trauma, surgery or illness), suppression of growth in children

Fluid and Electrolyte Disturbances: Fluid retention, potassium loss, hypertension, hypokalemic alkalosis, sodium retention

Gastrointestinal: Abdominal distention; elevation in serum liver enzyme levels (usually reversible upon discontinuation); hepatomegaly, hiccups, malaise, nausea, pancreatitis; peptic ulcer with possible perforation and hemorrhage; ulcerative esophagitis

General: Increased appetite and weight gain

Metabolic: Negative nitrogen balance due to protein catabolism

Musculoskeletal: Aseptic necrosis of femoral and humeral heads; charcot-like arthropathy, loss of muscle mass; muscle weakness; osteoporosis; pathologic fracture of long bones; steroid myopathy; tendon rupture; vertebral compression fractures

Neurological: Arachnoiditis, convulsions; depression, emotional instability, euphoria, headache; increased intracranial pressure with papilledema (pseudotumor cerebri) usually following discontinuation of treatment; insomnia, meningitis, mood swings, neuritis, neuropathy, paraparesis/paraplegia, paresthesia, personality changes, sensory disturbances, vertigo

Ophthalmic: Exophthalmos; glaucoma; increased intraocular pressure; posterior subcapsular cataracts

Reproductive: Alteration in motility and number of spermatozoa
Postmarketing Experience
Adverse reactions have been identified during post approval use of Orapred ODT. Because these reactions are reported voluntarily from a population of uncertain size, it is not always possible to reliably estimate their frequency or establish a causal relationship to drug exposure. The postmarketing experience has not raised new safety concerns beyond those already established for immediate-release prednisolone.

7 DRUG INTERACTIONS

- Aminoglutethimide: Aminoglutethimide may lead to loss of corticosteroid-induced adrenal suppression.
- Amphotericin B: There have been cases reported in which concomitant use of Amphotericin B and hydrocortisone was followed by cardiac enlargement and congestive heart failure (see also Potassium depleting agents).
- Anticholinesterase agents: Concomitant use of anticholinesterase agents and corticosteroids may produce severe weakness in patients with myasthenia gravis. If possible, anticholinesterase agents should be withdrawn at least 24 hours before initiating corticosteroid therapy.
- Anticoagulant agents: Co-administration of corticosteroids and warfarin usually results in inhibition of response to warfarin, although there have been some conflicting reports. Therefore, coagulation indices should be monitored frequently to maintain the desired anticoagulant effect.
- Antidiabetic Agents: Because corticosteroids may increase blood glucose concentrations, dosage adjustments of antidiabetic agents may be required.
- Antitubercular drugs: Serum concentrations of isoniazid may be decreased.
- CYP 3A4 inducers (e.g. barbiturates, phenytoin, carbamazepine, and rifampin): Drugs such as barbiturates, phenytoin, ephedrine, and rifampin, which induce hepatic microsomal drug metabolizing enzyme activity may enhance metabolism of prednisolone and require that the dosage of Orapred be increased.
- CYP 3A4 inhibitors (e.g., ketoconazole, macrolide antibiotics): Ketoconazole has been reported to decrease the metabolism of certain corticosteroids by up to 60% leading to an increased risk of corticosteroid side effects.
- Cholestyramine: Cholestyramine may increase the clearance of corticosteroids.
- Cyclosporine: Increased activity of both cyclosporine and corticosteroids may occur when the two are used concurrently. Convulsions have been reported with this concurrent use.
- Digitalis: Patients on digitalis glycosides may be at increased risk of arrhythmias due to hypokalemia.
- Estrogens, including oral contraceptives: Estrogens may decrease the hepatic metabolism of certain corticosteroids thereby increasing their effect.
- NSAIDS, including aspirin and salicylates: Concomitant use of aspirin or other non-steroidal anti-inflammatory agents and corticosteroids increases the risk of gastrointestinal side effects. Aspirin should be used cautiously in conjunction with corticosteroids in hypoprothrombinemia. The clearance of salicylates may be increased with concurrent use of corticosteroids.
- Potassium-depleting agents (e.g., diuretics, Amphotericin B): When corticosteroids are administered concomitantly with potassium-depleting agents, patients should be observed closely for development of hypokalemia.
- Skin Tests: Corticosteroids may suppress reactions to skin tests.
- Toxoids and live or inactivated Vaccines: Due to inhibition of antibody response, patients on prolonged corticosteroid therapy may exhibit a diminished response to toxoids and live or inactivated vaccines. Corticosteroids may also potentiate the replication of some organisms contained in live attenuated vaccines.

8 USE IN SPECIFIC POPULATIONS

8.1 Pregnancy

Risk Summary
Based on findings from human and animal studies, corticosteroids including Orapred, can cause fetal harm when administered to a pregnant woman (see Data) [see Warnings and Precautions (5.10)]. Published epidemiological studies suggest a small but inconsistent increased risk of orofacial clefts with use of corticosteroids during the first trimester. Intrauterine growth restriction and decreased birth weight have also been reported with maternal use of corticosteroids during pregnancy; however, the underlying maternal condition may also contribute to these risks (see Clinical Considerations). Published animal studies show prednisolone to be teratogenic in rats, rabbits, hamsters, and mice with increased incidence of cleft palate in offspring (see Data). Advise a pregnant woman about the potential harm to a fetus.
The estimated background risk of major birth defects and miscarriage for the indicated population is unknown. All pregnancies have a background risk of birth defect, loss, or other adverse outcomes. In the U.S. general population, the estimated background risk of major birth defects and miscarriages in clinically recognized pregnancies is 2 to 4% and 15 to 20%, respectively.
Clinical Considerations
Fetal/Neonatal Adverse Reactions
Infants born to pregnant women who have received corticosteroids should be carefully monitored for signs and symptoms of hypoadrenalism [see Warnings and Precautions (5.1)].
Data
Human Data
Published epidemiological studies on the association between prednisolone and fetal outcomes have reported inconsistent findings and have important methodological limitations. Multiple cohort and case-controlled studies in humans report that maternal corticosteroid use during the first trimester increases the incidence of cleft lip with or without cleft palate from about 1/1000 infants to 3-5/1000 infants; however, a risk for orofacial clefts has not been reported in all studies. Methodological limitations of these studies include non-randomized design, retrospective data collection, and the inability to control for confounders such as underlying maternal disease and use of concomitant medications.
Two prospective case control studies showed decreased birth weight in infants exposed to maternal corticosteroids in utero. In humans, the risk of decreased birth weight appears to be dose related and may be minimized by administering lower corticosteroid doses. It is likely that underlying maternal conditions contribute to intrauterine growth restriction and decreased birth weight, but it is unclear to what extent these maternal conditions contribute to the increased risk of orofacial clefts.
Animal Data
Published literature indicates prednisolone has been shown to be teratogenic in rats, rabbits, hamsters, and mice with increased incidence of cleft palate in offspring, supportive of the clinical data. In teratogenicity studies, cleft palate along with an elevation of fetal lethality (or increase in resorptions) and reductions in fetal body weight occurred in rats at maternal doses of 30 mg/kg (equivalent to 290 mg in a 60 kg individual based on mg/m^2 body surface comparison) and higher. Cleft palate was observed in mice at a maternal dose of 20 mg/kg (equivalent to 100 mg in a 60 kg individual based on mg/m^2 comparison). Additionally, constriction of the ductus arteriosus was observed in fetuses of pregnant rats exposed to prednisolone.

8.2 Lactation

Risk Summary
Prednisolone is present in human milk. Published reports suggest infant daily doses are estimated to be less than 1% of the maternal daily dose. No adverse effects in the breastfed infant have been reported following maternal administration of prednisolone during breastfeeding. There are no available data on the effects of prednisolone on milk production. High doses of corticosteroids administered to lactating women for long periods could potentially produce problems in the breastfed infant including growth and development and interfere with endogenous corticosteroid production (see Clinical Considerations) [see Use in Specific Populations (8.4)].The developmental and health benefits of breastfeeding should be considered along with the mother's clinical need for Orapred and any potential adverse effects on the breastfed child from Orapred or from the mother's underlying condition.
Clinical Considerations
In order to minimize exposure, the lowest dose should be prescribed to a lactating women to achieve the desired clinical effect.

8.4 Pediatric Use

The efficacy and safety of prednisolone in the pediatric population are based on the well-established course of effect of corticosteroids, which is similar in pediatric and adult populations. Published studies provide evidence of efficacy and safety in pediatric patients for the treatment of nephrotic syndrome (>2 years of age), and aggressive lymphomas and leukemias (>1 month of age). However, some of these conclusions and other indications for pediatric use of corticosteroid, e.g., severe asthma and wheezing, are based on adequate and well-controlled trials conducted in adults, on the premises that the course of the diseases and their pathophysiology are considered to be substantially similar in both populations.

The adverse effects of prednisolone in pediatric patients are similar to those in adults [see Adverse Reactions (6)]. Like adults, pediatric patients should be carefully observed with frequent measurements of blood pressure, weight, height, intraocular pressure, and clinical evaluation for the presence of infection, psychosocial disturbances, thromboembolism, peptic ulcers, cataracts, and osteoporosis. Children, who are treated with corticosteroids by any route, including systemically administered corticosteroids, may experience a decrease in their growth velocity. This negative impact of corticosteroids on growth has been observed at low systemic doses and in the absence of laboratory evidence of HPA axis suppression (i.e., cosyntropin stimulation and basal cortisol plasma levels).

Growth velocity may therefore be a more sensitive indicator of systemic corticosteroid exposure in children than some commonly used tests of HPA axis function. The linear growth of children treated with corticosteroids by any route should be monitored, and the potential growth effects of prolonged treatment should be weighed against clinical benefits obtained and the availability of other treatment alternatives. In order to minimize the potential growth effects of corticosteroids, children should be titrated to the lowest effective dose.

8.5 Geriatric Use

No overall differences in safety or effectiveness were observed between elderly subjects and younger subjects, and other reported clinical experience with prednisolone has not identified differences in responses between the elderly and younger patients. However, the incidence of corticosteroid-induced side effects may be increased in geriatric patients and appear to be dose-related. Osteoporosis is the most frequently encountered complication, which occurs at a higher incidence rate in corticosteroid-treated geriatric patients as compared to younger populations and in age-matched controls. Losses of bone mineral density appear to be greatest early on in the course of treatment and may recover over time after steroid withdrawal or use of lower doses (i.e., ≤5 mg/day). Prednisolone doses of 7.5 mg/day or higher, have been associated with an increased relative risk of both vertebral and nonvertebral fractures, even in the presence of higher bone density compared to patients with involutional osteoporosis.

Routine screening of geriatric patients, including regular assessments of bone mineral density and institution of fracture prevention strategies, along with regular review of Orapred indication should be undertaken to minimize complications and keep the Orapred dose at the lowest acceptable level. Co-administration of bisphosphonates has been shown to retard the rate of bone loss in corticosteroid-treated males and postmenopausal females, and these agents are recommended in the prevention and treatment of corticosteroid-induced osteoporosis.

It has been reported that equivalent weight-based doses yield higher total and unbound prednisolone plasma concentrations and reduced renal and non-renal clearance in elderly patients compared to younger populations. However, it is not clear whether dosing reductions would be necessary in elderly patients, since these pharmacokinetic alterations may be offset by age-related differences in responsiveness of target organs and/or less pronounced suppression of adrenal release of cortisol. Dose selection for an elderly patient should be cautious, usually starting at the low end of the dosing range, reflecting the greater frequency of decreased hepatic, renal, or cardiac function, and of concomitant disease or other drug therapy.

This drug is known to be substantially excreted by the kidney, and the risk of toxic reactions to this drug may be greater in patients with impaired renal function. Because elderly patients are more likely to have decreased renal function, care should be taken in dose selection, and it may be useful to monitor renal function.

10 OVERDOSAGE

The effects of accidental ingestion of large quantities of prednisolone over a very short period of time have not been reported, but prolonged use of the drug can produce mental symptoms, moon face, abnormal fat deposits, fluid retention, excessive appetite, weight gain, hypertrichosis, acne, striae, ecchymosis, increased sweating, pigmentation, dry scaly skin, thinning scalp hair, increased blood pressure, tachycardia, thrombophlebitis, decreased resistance to infection, negative nitrogen balance with delayed bone and wound healing, headache, weakness, menstrual disorders, accentuated menopausal symptoms, neuropathy, fractures, osteoporosis, peptic ulcer, decreased glucose tolerance, hypokalemia, and adrenal insufficiency. Hepatomegaly and abdominal distention have been observed in children.

Treatment of acute overdosage is by immediate gastric lavage or emesis followed by supportive and symptomatic therapy. For chronic overdosage in the face of severe disease requiring continuous steroid therapy, the dosage of prednisolone may be reduced only temporarily, or alternate day treatment may be introduced.

11 DESCRIPTION

Orapred ODT (prednisolone sodium phosphate disintegrating tablets) is a sodium salt of the phosphoester of the glucocorticoid prednisolone. Glucocorticoids are adrenocortical steroids, both naturally occurring and synthetic, which are readily absorbed from the gastrointestinal tract.

Prednisolone sodium phosphate occurs as white or slightly yellow, friable granules or powder. It is freely soluble in water; soluble in methanol; slightly soluble in alcohol and in chloroform; and very slightly soluble in acetone and in dioxane.

The chemical name of prednisolone sodium phosphate is pregna-1, 4-diene-3, 20-dione, 11, 17-dihydroxy-21-(phosphonooxy)-, disodium salt, (11ß)-.
The empirical formula is C21H27Na2O8P; the molecular weight is 484.39. Its chemical structure is:

Each orally disintegrating tablet also contains the following inactive ingredients: citric acid, colloidal silicon dioxide, crospovidone, grape flavor, hypromellose, magnesium stearate, mannitol, methacrylate copolymer, microcrystalline cellulose, sodium bicarbonate, sucralose, and sucrose.

12 CLINICAL PHARMACOLOGY

12.1 Mechanism of Action

Prednisolone is a synthetic adrenocortical steroid drug with predominantly glucocorticoid properties. Some of these properties reproduce the physiological actions of endogenous glucocorticosteroids, but others do not necessarily reflect any of the adrenal hormones' normal functions; they are seen only after administration of large therapeutic doses of the drug. The pharmacological effects of prednisolone which are due to its glucocorticoid properties include: promotion of gluconeogenesis; increased deposition of glycogen in the liver; inhibition of the utilization of glucose; anti-insulin activity; increased catabolism of protein; increased lipolysis; stimulation of fat synthesis and storage; increased glomerular filtration rate and resulting increase in urinary excretion of urate (creatinine excretion remains unchanged); and increased calcium excretion. Depressed production of eosinophils and lymphocytes occurs, but erythropoiesis and production of polymorphonuclear leukocytes are stimulated. Inflammatory processes (edema, fibrin deposition, capillary dilatation, migration of leukocytes and phagocytosis) and the later stages of wound healing (capillary proliferation, deposition of collagen, cicatrization) are inhibited. Prednisolone can stimulate secretion of various components of gastric juice. Suppression of the production of corticotropin may lead to suppression of endogenous corticosteroids. Prednisolone has slight mineralocorticoid activity, whereby entry of sodium into cells and loss of intracellular potassium is stimulated. This is particularly evident in the kidney, where rapid ion exchange leads to sodium retention and hypertension.

12.3 Pharmacokinetics

Absorption:
Oral administration of single doses of 30 mg prednisolone base equivalent of Orapred ODT, and Pediapred Solution to 21 adult volunteers yielded comparable pharmacokinetic data:

Table 1. Comparison of Mean Pharmacokinetic Parameters (%CV) in Healthy Volunteers Following a Single Dose of 30 mg Orapred ODT and Pediapred Solution,
Dose [Administered under fasting conditions.] | AUC0-∞ (ng∙hr/mL) | Cmax (ng∙hr/mL) [Mean values of 21 normal volunteers]
(30 mg prednisolone base equivalent) | (± S.D.) | (± S.D.)
Pediapred Solution | 2426.1 (360.0) | 461.33 (77.94)
Orapred ODT | 2408.1 (361.5) | 420.91 (78.28)

Distribution:
Prednisolone is 70-90% protein-bound in the plasma and the volume of distribution is reported as 0.22 - 0.7 L/kg.

Metabolism:
Prednisolone is reported to be metabolized mainly in the liver and excreted in the urine as sulfate and glucuronide conjugates.

Excretion:
Prednisolone is eliminated from the plasma with a mean (± SD) half-life of 2.6 (± 0.27) hours.

Special Populations
The systemic availability, metabolism and elimination of prednisolone after administration of single weight-based doses (0.8 mg/kg) of intravenous (IV) prednisolone and oral prednisone were reported in a small study of 19 younger (23 to 34 years) and 12 geriatric (65 to 89 years) subjects. Results showed that the systemic availability of total and unbound prednisolone, as well as interconversion between prednisolone and prednisone were independent of age. The mean unbound fraction of prednisolone was higher, and the steady-state volume of distribution (Vss) of unbound prednisolone was reduced in elderly patients. Plasma prednisolone concentrations were higher in elderly subjects, and the higher AUCs of total and unbound prednisolone were most likely reflective of an impaired metabolic clearance, evidenced by reduced fractional urinary clearance of 6b-hydroxyprednisolone. Despite these findings of higher total and unbound prednisolone concentrations, elderly subjects had higher AUCs of cortisol, suggesting that the elderly population is less sensitive to suppression of endogenous cortisol or their capacity for hepatic inactivation of cortisol is diminished.

13 NONCLINICAL TOXICOLOGY

13.1 Carcinogenesis, Mutagenesis, Impairment of Fertility

Orapred was not formally evaluated in carcinogenicity studies. Review of the published literature identified the potential for malignancy at doses within the therapeutic range. In a 2-year study, male Sprague-Dawley rats administered prednisolone in drinking water at an estimated continuous daily prednisolone consumption of 368 mcg/kg/day (equivalent to 3.5 mg/day in a 60 kg individual based on an mg/m^2 body surface area comparison) developed increased incidences of hepatic adenomas. However infrequent administration of prednisolone did not result in malignancy. In an 18-month study, intermittent (1, 2, 4.5 or 9 times per month) oral gavage of 3 mg/kg prednisolone did not induce tumors in female Sprague-Dawley rats (equivalent to 29 mg in a 60 kg individual based on a mg/m^2 body surface area comparison).

Orapred was not formally evaluated for genotoxicity. However, in published studies prednisolone was not mutagenic with or without metabolic activation in the Ames bacterial reverse mutation assay using Salmonella typhimurium and Escherichia coli, or in a mammalian cell gene mutation assay using mouse lymphoma L5178Y cells, according to current evaluation standards. In a published chromosomal aberration study in Chinese Hamster Lung (CHL) cells, a slight increase was seen in the incidence of structural chromosomal aberrations with metabolic activation at the highest concentration tested, however, the effect appears to be equivocal.

Orapred was not formally evaluated in fertility studies. However, alterations in motility and numbers of spermatozoa, and menstrual irregularities have been described with clinical use [see Adverse Reactions (6)].

16 HOW SUPPLIED/STORAGE AND HANDLING

Orapred ODT (prednisolone sodium phosphate orally disintegrating tablets) 13.4 mg prednisolone sodium phosphate (equivalent to 10 mg prednisolone base) is a white, flat faced, beveled tablet, debossed with ORA on one side and 10 on the other. Supplied as:

- NDC 59212-700-12: 12 tablets per carton. Each carton has 2 cards containing 6 tablets.

Orapred ODT (prednisolone sodium phosphate orally disintegrating tablets) 20.2 mg prednisolone sodium phosphate (equivalent to 15 mg prednisolone base) is a white, flat faced, beveled tablet, debossed with ORA on one side and 15 on the other. Supplied as:

- NDC 59212-701-12: 12 tablets per carton. Each carton has 2 cards containing 6 tablets.

Orapred ODT: (prednisolone sodium phosphate orally disintegrating tablets) 40.3 mg prednisolone sodium phosphate (equivalent to 30 mg prednisolone base) is a white, flat faced, beveled tablet, debossed with ORA on one side and 30 on the other. Supplied as:

- NDC 59212-702-12: 12 tablets per carton. Each carton has 2 cards containing 6 tablets.

STORAGE AND HANDLING

Store at 20° to 25°C (68° to 77°F); excursions permitted to 15° to 30°C (59° to 86°F). [See USP controlled Room Temperature]. Protect from moisture.

Do not break or use partial Orapred ODT tablets. Keep out of the reach of children.

17 PATIENT COUNSELING INFORMATION

Advise patients not to discontinue the use of Orapred abruptly or without medical supervision, to advise any healthcare provider that they are taking it, and to seek medical advice at once should they develop fever or other signs of infection. Inform patients to take Orapred exactly as prescribed, follow the instructions on the prescription label, and not stop taking Orapred without first checking with their health-care providers, as there may be a need for gradual dose reduction.

Patients should discuss with their physician if they have had recent or ongoing infections or if they have recently received a vaccine.

Warn patients who are on immunosuppressant doses of corticosteroids to avoid exposure to chickenpox or measles. Advise patients that if they are exposed, to seek medical advice without delay.

There are a number of medicines that can interact with Orapred. Patients should inform their healthcare provider of all the medicines they are taking, including over-the counter and prescription medicines (such as phenytoin, diuretics, digitalis or digoxin, rifampin, amphotericin B, cyclosporine, insulin or diabetes medicines, ketoconazole, estrogens including birth control pills and hormone replacement therapy, blood thinners such as warfarin, aspirin or other NSAIDS, barbiturates), dietary supplements, and herbal products. If patients are taking any of these drugs, alternate therapy, dosage adjustment, and/or a special test may be needed during the treatment.

For missed doses, inform patients to take the missed dose as soon as they remember. If it is almost time for the next dose, the missed dose should be skipped and the medicine taken at the next regularly scheduled time. Advise patients not to take an extra dose to make up for the missed dose.

Inform patients to take Orapred with food to avoid GI irritation.

Advise patients of common adverse reactions that could occur with Orapred use to include fluid retention, alteration in glucose tolerance, elevation in blood pressure, behavioral and mood changes, increased appetite and weight gain.
Advise pregnant women and females of reproductive potential of the potential risk to a fetus. Advise females to inform their healthcare provider of a known or a suspected pregnancy. [see Warnings and Precautions (5.10) and Use in Specific Populations (8.1)].

Orapred ODT tablets are packaged in a blister. Patients should be instructed not to remove the tablet from the blister until just prior to dosing. The blister pack should then be peeled open, and the orally disintegrating tablet placed on the tongue, where the tablets may be swallowed whole as any conventional tablet, or allowed to dissolve in the mouth, with or without the assistance of water. Orally disintegrating tablet dosage forms are friable and are not intended to be cut, split, or broken.

Manufactured for:
Advanz Pharma (US) Corp.
Bannockburn, IL 60015
US Patent No. 6,740,341
“ORAPRED® is a registered trademark of Mercury Pharma Group Limited. Distributed by Advanz Pharma (US) Corp. under license.”
For inquiries call 1-877-370-1142

10 mg Carton

Rx only

NDC 59212-700-12

Contents: 2 cards containing 6 tablets
Grape Flavor
Orapred ODT®
(prednisolone sodium phosphate orally disintegrating tablets)
Equivalent to prednisolone 10mg

15 mg Carton

Rx only

NDC 59212-701-12

Contents: 2 cards containing 6 tablets
Grape Flavor
Orapred ODT®
(prednisolone sodium phosphate orally disintegrating tablets)
Equivalent to prednisolone 15mg

30 mg Carton

Rx only

NDC 59212-702-12

Contents: 2 cards containing 6 tablets
Grape Flavor
Orapred ODT®
(prednisolone sodium phosphate orally disintegrating tablets)
Equivalent to prednisolone 30mg